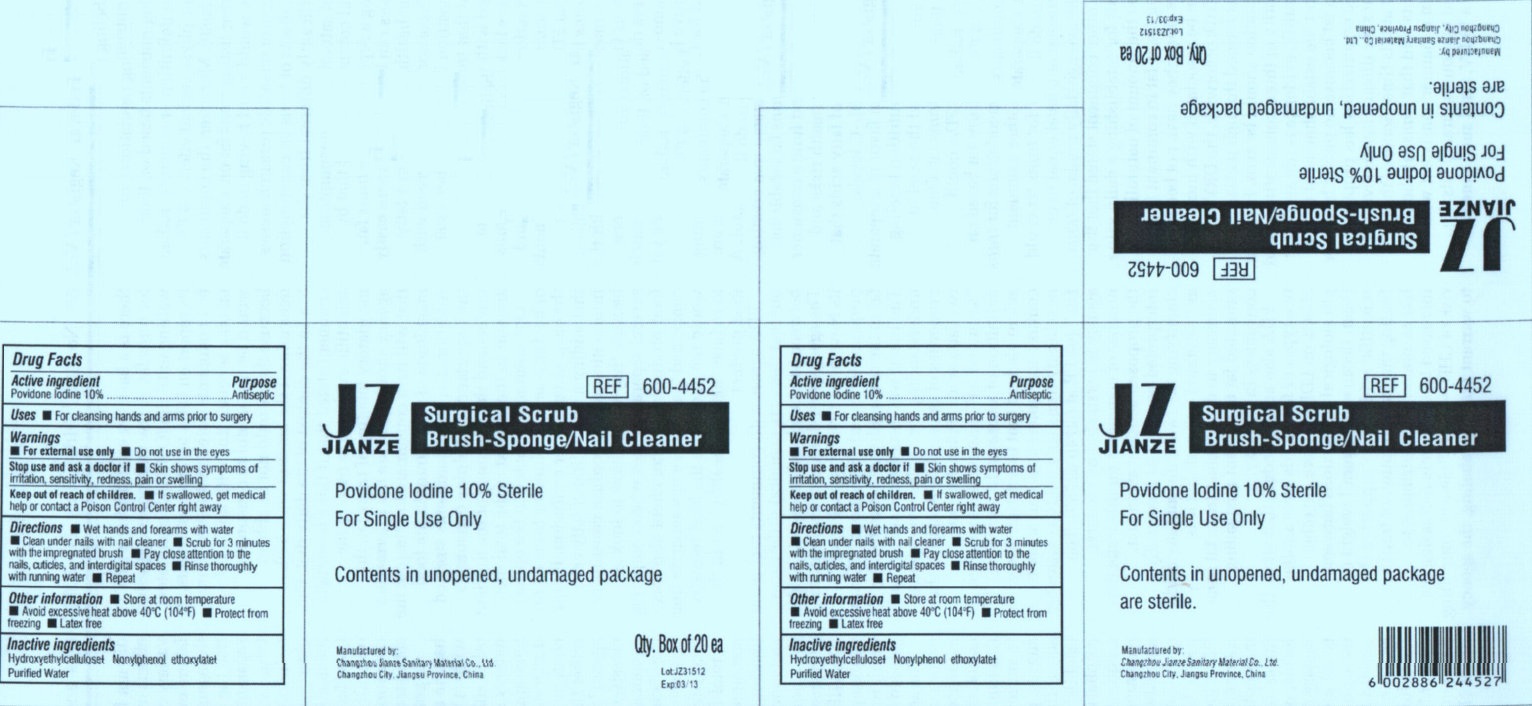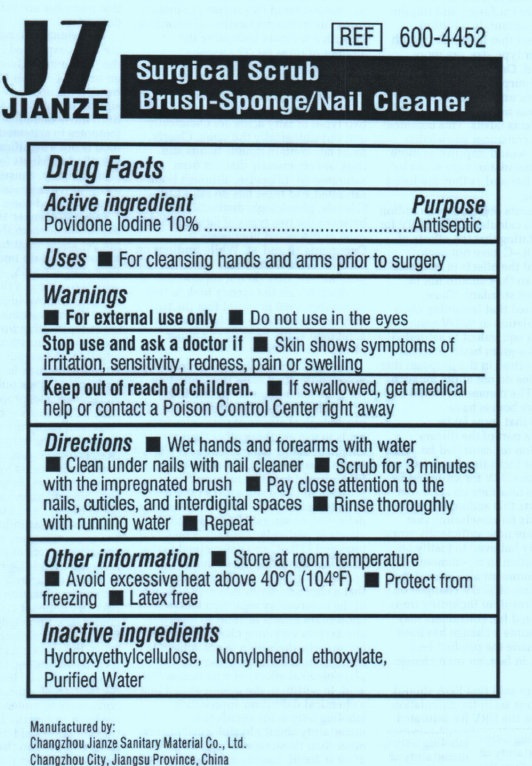 DRUG LABEL: JIANZE SURGICAL SCRUB BRUSH NAIL CLEANER
NDC: 50666-003 | Form: SPONGE
Manufacturer: Changzhou Jianze Sanitary Material Co., Ltd.
Category: otc | Type: HUMAN OTC DRUG LABEL
Date: 20120611

ACTIVE INGREDIENTS: POVIDONE-IODINE 2 g/20 g
INACTIVE INGREDIENTS: WATER; HYDROXYETHYL CELLULOSE (100 MPA.S AT 2%)

JIANZE SURGICAL SCRUB BRUSH-SPONGE / NAIL CLEANER

Active Ingredient

Povidone Iodine 10%

Purpose

Antiseptic

Uses

- For cleansing hands and arms prior to surgery

Warnings

- For external use only
- Do not use in the eyes

Stop use and ask a doctor if

- skin shows symptoms of irritation, sensitivity, redness, pain or swelling

Keep out of reach of children.

- If swallowed, get medical help or contact a Poison Control Center right away

Directions

- Wet hands and forearms with water
- Clean under nails with nail cleaner
- Scrub for 3 minutes with the impregnated brush
- Pay close attention to nails, cuticles, and interdigital spaces
- Rinse thoroughly with running water
- Repeat

Other Information

- Store at room temperature
- Avoid excessive heat above 40 degrees C (104 degrees F)
- Protect from freezing
- Latex free

Inactive Ingredients

Hydroxyethylcellulose

Nonylphenol Ethoxylate

Purified Water